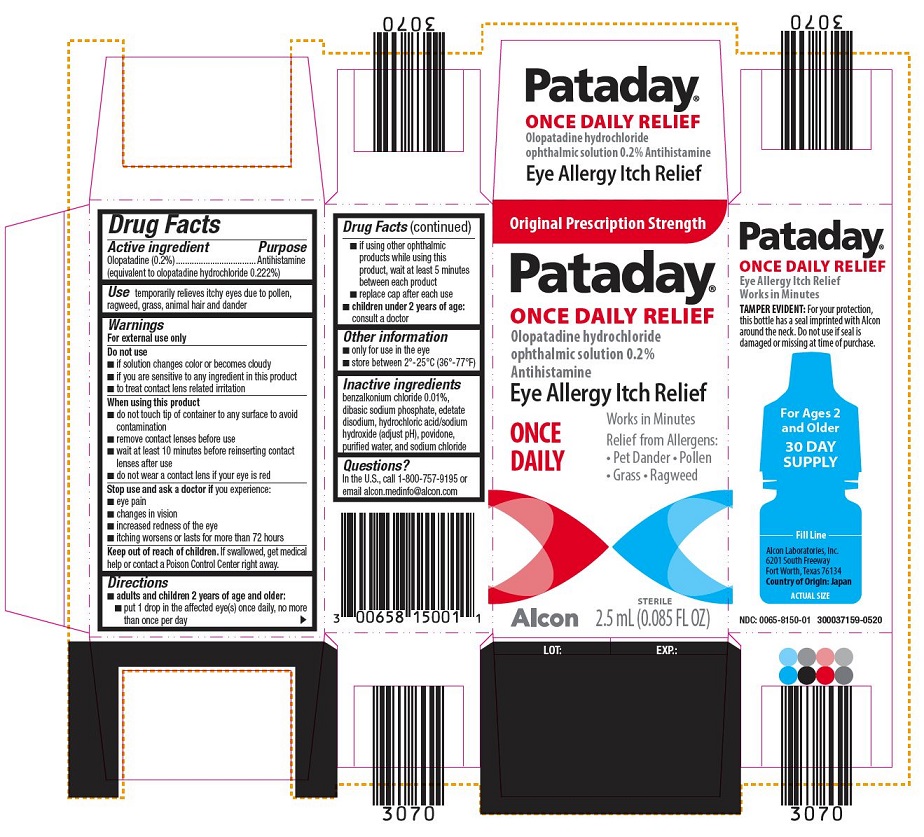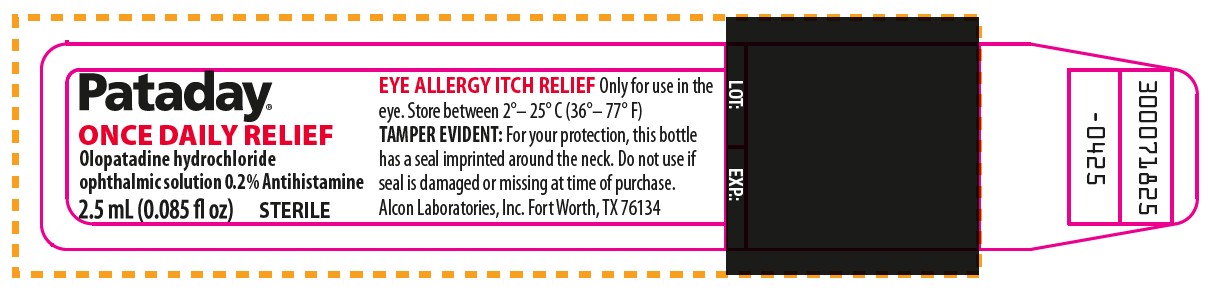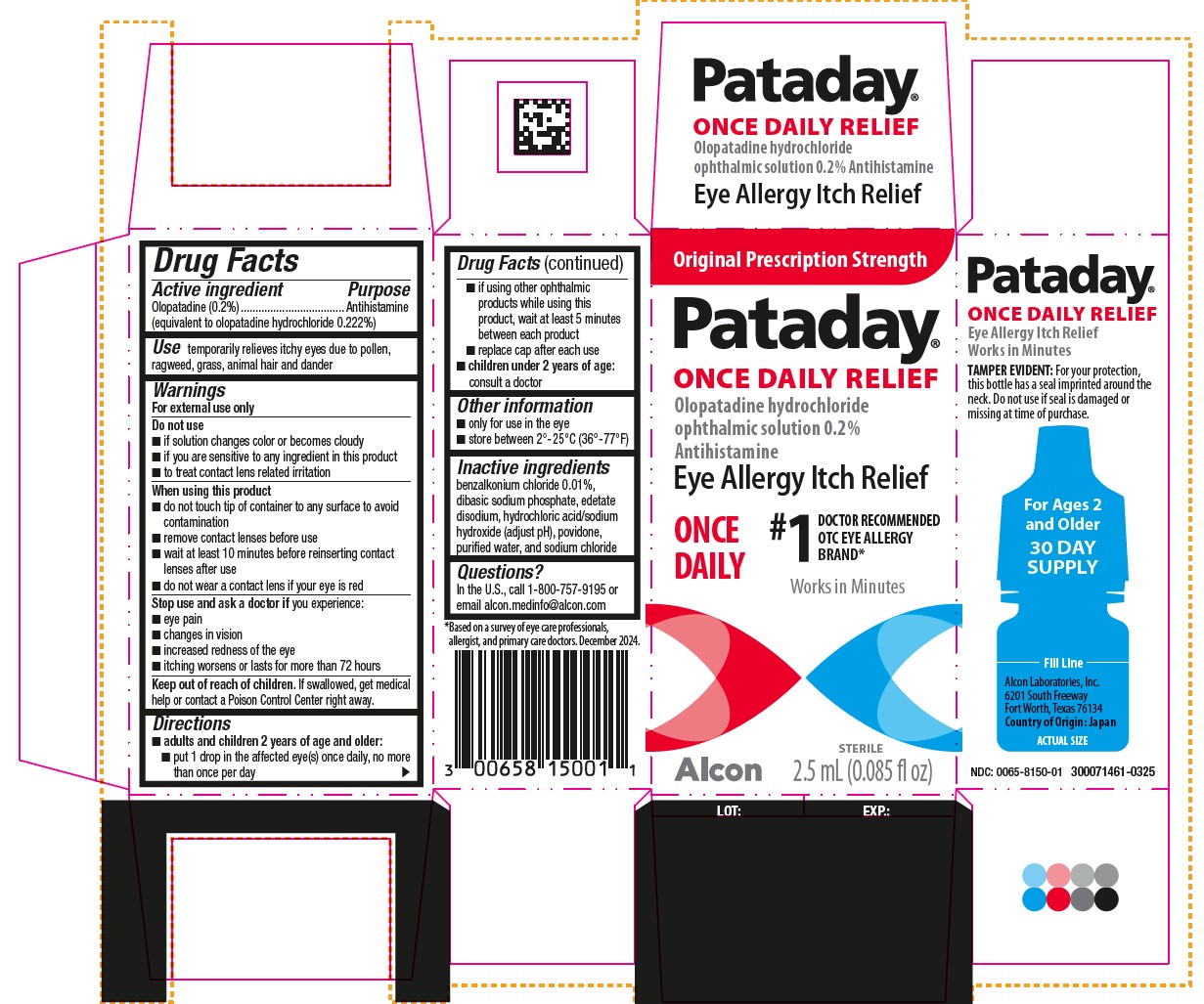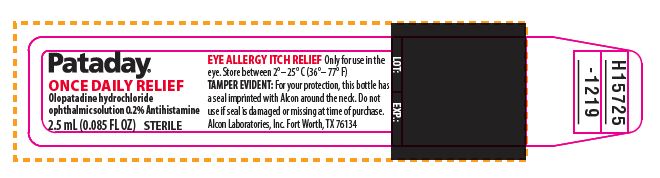 DRUG LABEL: PATADAY ONCE DAILY RELIEF
NDC: 0065-8150 | Form: SOLUTION
Manufacturer: Alcon Laboratories, Inc.
Category: otc | Type: HUMAN OTC DRUG LABEL
Date: 20260120

ACTIVE INGREDIENTS: Olopatadine Hydrochloride 2 mg/1 mL
INACTIVE INGREDIENTS: Povidone, Unspecified; Sodium Phosphate, Dibasic, Unspecified Form; Sodium Chloride; Edetate Disodium; Benzalkonium Chloride; Hydrochloric Acid; Sodium Hydroxide; Water

Drug Facts

ACTIVE INGREDIENT

Active Ingredients | Purpose
Olopatadine 0.2% (equivalent to olopatadine hydrochloride 0.222%) | Antihistamine

INDICATIONS AND USAGE

Use temporarily relieves itchy eyes due to pollen, ragweed, grass, animal hair and dander

Warnings
For external use only

Do not use

- if solution changes color or becomes cloudy
- if you are sensitive to any ingredient in this product
- to treat contact lens related irritation

When using this product

- do not touch tip of container to any surface to avoid contamination
- remove contact lenses before use
- wait at least 10 minutes before reinserting contact lenses after use
- do not wear a contact lens if your eye is red

Stop use and ask a doctor if you experience:

- eye pain
- changes in vision
- increased redness of the eye
- itching worsens or lasts for more than 72 hours

Keep out of reach of children. If swallowed, get medical help or contact a Poison Control Center right away.

Directions

- adults and children 2 years of age and older:
  - put 1 drop in the affected eye(s) once daily, no more than once per day
  - if using other ophthalmic products while using this product, wait at least 5 minutes between each product
  - replace cap after each use
- children under 2 years of age: consult a doctor

Other information

- only for use in the eye
- store between 2°-25°C (36°-77°F)

Inactive ingredients

benzalkonium chloride 0.01%, dibasic sodium phosphate, edetate disodium, hydrochloric acid/sodium hydroxide (adjust pH), povidone, purified water, and sodium chloride

Questions?

In the U.S., call 1-800-757-9195 or email alcon.medinfo@alcon.com

PRINCIPAL DISPLAY PANEL

Pataday®
ONCE DAILY RELIEF
Olopatadine hydrochloride
ophthalmic solution 0.2% Antihistamine
2.5 mL (0.085 FL OZ)
STERILE
EYE ALLERGY ITCH RELIEF
Only for use in the eye. Store between 2°– 25° C (36°– 77° F)
TAMPER EVIDENT: For your protection, this bottle has a seal imprinted with Alcon around the neck. Do not use if seal is damaged or missing at time of purchase.
Alcon Laboratories, Inc.
Fort Worth, TX 76134
LOT: EXP.:
H15725-219

Original Prescription Strength
Pataday
ONCE DAILY RELIEF
Olopatadine hydrochloride
ophthalmic solution 0.2%
Antihistamine
Eye Allergy Itch Relief
ONCE DAILY
Works in Minutes Relief from Allergens:

- Pet Dander
- Pollen
- Grass
- Ragweed

STERILE
2.5 mL (0.085 FL OZ)
Alcon
Pataday
ONCE DAILY RELIEF
Eye Allergy Itch Relief
Works in Minutes
TAMPER EVIDENT: For your protection,
this bottle has a seal imprinted with Alcon
around the neck. Do not use if seal is
damaged or missing at time of purchase.
For Ages 2
and Older
30 DAY
SUPPLY
________Fill Line________
Alcon Laboratories, Inc.
6201 South Freeway
Fort Worth, Texas 76134
Country of Origin: Japan
ACTUAL SIZE
NDC: 0065-6150-01 300037159-0520

Pataday®
ONCE DAILY RELIEF
Olopatadine hydrochloride
ophthalmic solution 0.2% Antihistamine
2.5 mL (0.085 fl oz) STERILE
EYE ALLERGY ITCH RELIEF Only for use in the
eye. Store between 2°– 25° C (36°– 77° F)
TAMPER EVIDENT: For your protection, this bottle
has a seal imprinted around the neck. Do not use if
seal is damaged or missing at time of purchase.
Alcon Laboratories, Inc. Fort Worth, TX 76134
LOT: EXP.:
300071825
-0425

Original Prescription Strength
Pataday®
ONCE DAILY RELIEF
Olopatadine hydrochloride
ophthalmic solution 0.2%
Antihistamine
Eye Allergy Itch Relief
ONCE
DAILY
#1 DOCTOR RECOMMENDED
OTC EYE ALLERGY
BRAND*
Works in Minutes
Alcon
STERILE
2.5 mL (0.085 fl oz)
LOT: EXP:
Pataday®
ONCE DAILY RELIEF
Olopatadine hydrochloride
ophthalmic solution 0.7% Antihistamine
Eye Allergy Itch Relief
Pataday®
ONCE DAILY RELIEF
Eye Allergy Itch Relief
Works in minutesTAMPER EVIDENT: For your protection,
this bottle has a seal imprinted around the
neck. Do not use if seal is damaged or
missing at time of purchase.
For Ages 2
and older
30 DAY
SUPPLY
________Fill Line________
Alcon Laboratories, Inc.
6201 South Freeway
Fort Worth, Texas 76134
Country of Origin: Japan
ACTUAL SIZE
NDC: 0065-8150-01 300071461-0325
*Based on a survey of eye care professionals,
allergist, and primary care doctors. December 2024.